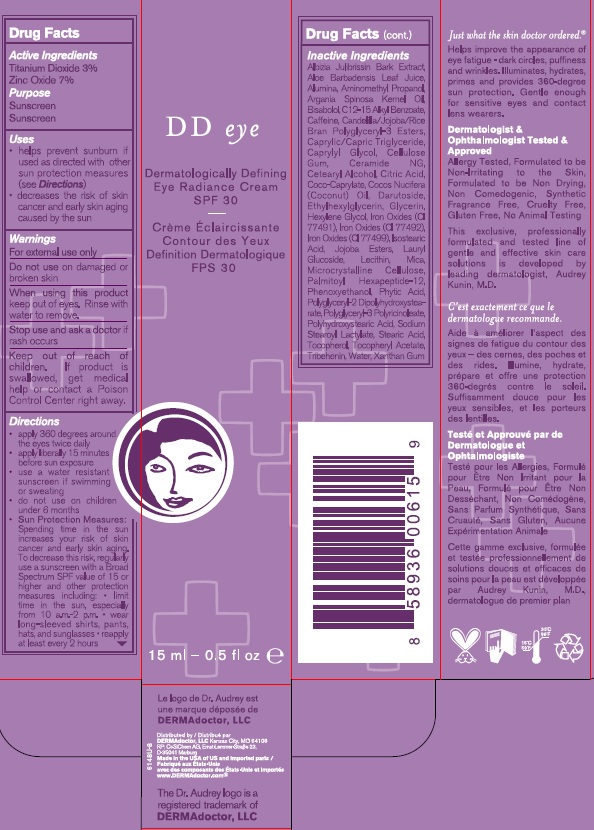 DRUG LABEL: DermaDoctor DD Eye
NDC: 68715-367 | Form: CREAM
Manufacturer: DERMAdoctor
Category: otc | Type: HUMAN OTC DRUG LABEL
Date: 20210628

ACTIVE INGREDIENTS: zinc oxide 7 g/100.0 mL; TITANIUM DIOXIDE 3 g/100.0 mL
INACTIVE INGREDIENTS: ALBIZIA JULIBRISSIN BARK; ALOE VERA WHOLE; ALUMINUM OXIDE; AMINOMETHYL PROPANEDIOL; ARGANIA SPINOSA SEED; LEVOMENOL; ALKYL (C12-15) BENZOATE; CAFFEINE; MEDIUM-CHAIN TRIGLYCERIDES; CAPRYLYL GLYCOL; CARBOXYMETHYLCELLULOSE SODIUM, UNSPECIFIED FORM; CERAMIDE NG; CETOSTEARYL ALCOHOL; CITRIC ACID MONOHYDRATE; COCO-CAPRYLATE; COCONUT OIL; DARUTOSIDE; ETHYLHEXYLGLYCERIN; GLYCERIN; HEXYLENE GLYCOL; FERROSOFERRIC OXIDE; FERRIC OXIDE RED; FERRIC OXIDE YELLOW; ISOSTEARIC ACID; JOJOBA OIL, RANDOMIZED; LAURYL GLUCOSIDE; LECITHIN, SOYBEAN; MICA; MICROCRYSTALLINE CELLULOSE; PALMITOYL HEXAPEPTIDE-12; PHENOXYETHANOL; FYTIC ACID; POLYGLYCERYL-2 DIPOLYHYDROXYSTEARATE; POLYGLYCERYL-3 RICINOLEATE; POLYHYDROXYSTEARIC ACID (2300 MW); SODIUM STEAROYL LACTYLATE; STEARIC ACID; TOCOPHEROL; .ALPHA.-TOCOPHEROL ACETATE, DL-; TRIBEHENIN; water; XANTHAN GUM

DD Eye Dermatologically Defining Eye Radiance Cream SPF 30

Active Ingredients

Titanium Dioxide 3%

Zinc Oxide 7%

Purpose

Sunscreen

Uses

- helps prevent sunburn if used as directed with other sun protection measures (seeDirections)
- decreases the risk of skin cancer and early skin aging caused by the sun

Warnings

For external use only

Do not use

on damaged or broken skin

When using this product

keep out of eyes. Rinse with water to remove

Stop use

and ask a doctor if rash occurs

Keep out of reach

of Children. If product is swallowed, get medical help or contact a Poinson Control Center right away

Directions

- apply 360 degrees around the eyes twice daily
- apply lierally 15 minutes before sun exposure
- use a water resistant sunscreen if swimming or sweating
- do not use on children under 6 months.
- Sun Protection Measures. Spending time in the sun increases your risk of skin cancer and early skin aging. To decrease this risk, regularly use a sunscreen with Broad Spectrum SPF value of 15 or higher and other protection measures including
- limit time in the sun,especially from 10 a.m.-2 p.m.
- wear long sleeved shirts, pants, hats and sunglasses
- reapply at least every 2 hours.

Inactive Ingredients

Albizia Julibrissin Bark Extract, Aloe Barbadensis Leaf Juice, Alumina, Aminomethyl Propanol, Argania Spinosa Kernel Oil, Bisabolol, C12-15 Alkyl Benzoate, Caffeine, Candelilla/Jojoba/Rice Bran Polyglyceryl-3 Esters, Caprylic/Capric Triglyceride, Caprylyl Glycol, Cellulose Gum, Ceramide NG, Cetearyl Alcohol, Citric Acid, Coco-Caprylate, Cocos Nucifera (Coconut) Oil, Darutoside, Ethylhexylglycerin, Glycerin, Hexylene Glycol, Iron Oxides (CI 77491), Iron Oxides (CI 77492), Iron Oxides (CI 77499), Isostearic Acid, Jojoba Esters, Lauryl Glucoside, Lecithin, Mica, Microcrystalline Cellulose,
Palmitoyl Hexapeptide-12, Phenoxyethanol, Phytic Acid, Polyglyceryl-2 Dipolyhydroxystearate, Polyglyceryl-3 Polyricinoleate, Polyhydroxystearic Acid, Sodium Stearoyl Lactylate, Stearic Acid, Tocopherol, Tocopheryl Acetate, Tribehenin, Water, Xanthan Gum